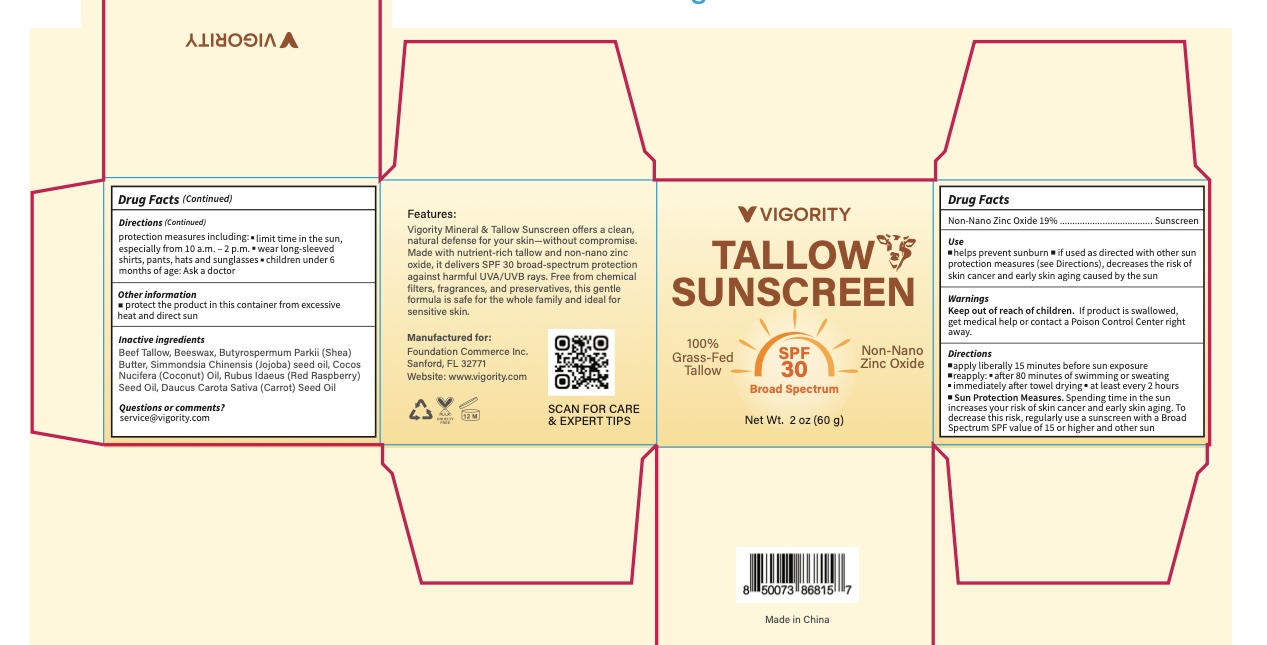 DRUG LABEL: Vigority Tallow Sunscreen SPF30
NDC: 85739-006 | Form: CREAM
Manufacturer: FOUNDATION COMMERCE INC
Category: otc | Type: HUMAN OTC DRUG LABEL
Date: 20250801

ACTIVE INGREDIENTS: ZINC OXIDE 19 g/100 g
INACTIVE INGREDIENTS: COCOS NUCIFERA (COCONUT) OIL; BEESWAX; BUTYROSPERMUM PARKII (SHEA) BUTTER; DAUCUS CAROTA SATIVA (CARROT) SEED OIL; BEEF TALLOW; RUBUS IDAEUS (RASPBERRY) SEED OIL; SIMMONDSIA CHINENSIS (JOJOBA) SEED OIL

Initial Drug Listing - Tallow Sunscreen SPF30 Jar

ACTIVE INGREDIENT

Non-Nano Zinc Oxide 19%

PURPOSE

Sunscreen

INDICATIONS AND USAGE

- helps prevent sunburn
- if used as directed with other sun protection measures (see Directions), decreases the risk of skin cancer and early skin aging caused by the sun

WARNINGS

For external use only

Keep out of reach of children. If product is swallowed, get medical help or contact a Poison Control Center right away.

DOSAGE AND ADMINISTRATION

- apply liberally 15 minutes before sun exposure
- reapply: - after 80 minutes of swimming or sweating - immediately after towel drying - at least every 2 hours
- Sun Protection Measures. Spending time in the sun increases your risk of skin cancer and early skin aging. To decrease this risk, regularly use a sunscreen with a Broad Spectrum SPF value of 15 or higher and other sun protection measures including:
- limit time in the sun, especially from 10 a.m. - 2 p.m.
- wear long-sleeved shirts, pants, hats and sunglasses
- children under 6 months of age: Ask a doctor

OTHER SAFETY INFORMATION

protect the product in this container from excessive heat and direct sun

INACTIVE INGREDIENT

Beef Tallow, Beeswax, Butyrospermum Parkii (Shea) Butter, Simmondsia Chinensis (Jojoba) seed oil, Cocos Nucifera (Coconut) Oil, Rubus Idaeus (Red Raspberry) Seed Oil, Daucus Carota Sativa (Carrot) Seed Oil

QUESTIONS

service@vigority.com